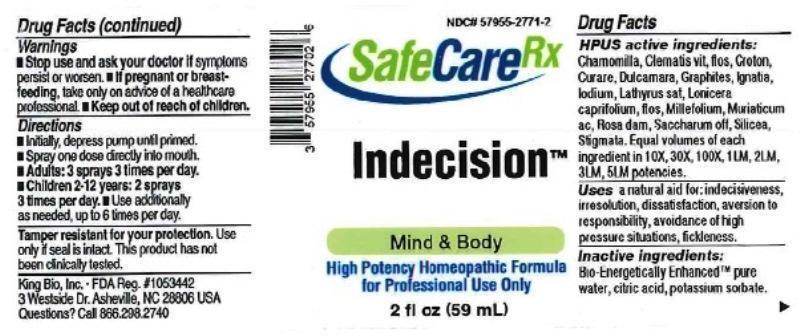 DRUG LABEL: Indecision
NDC: 57955-2771 | Form: LIQUID
Manufacturer: King Bio Inc.
Category: homeopathic | Type: HUMAN OTC DRUG LABEL
Date: 20161202

ACTIVE INGREDIENTS: MATRICARIA RECUTITA 10 [hp_X]/59 mL; CLEMATIS VITALBA FLOWER 10 [hp_X]/59 mL; CROTON TIGLIUM SEED 10 [hp_X]/59 mL; TUBOCURARINE CHLORIDE 10 [hp_X]/59 mL; SOLANUM DULCAMARA TOP 10 [hp_X]/59 mL; GRAPHITE 10 [hp_X]/59 mL; STRYCHNOS IGNATII SEED 10 [hp_X]/59 mL; IODINE 10 [hp_X]/59 mL; LATHYRUS SATIVAS SEED 10 [hp_X]/59 mL; LONICERA CAPRIFOLIUM FLOWERING TOP 10 [hp_X]/59 mL; ACHILLEA MILLEFOLIUM 10 [hp_X]/59 mL; HYDROCHLORIC ACID 10 [hp_X]/59 mL; ROSA DAMASCENA FLOWERING TOP 10 [hp_X]/59 mL; SUCROSE 10 [hp_X]/59 mL; SILICON DIOXIDE 10 [hp_X]/59 mL; CORN SILK 10 [hp_X]/59 mL
INACTIVE INGREDIENTS: WATER; ANHYDROUS CITRIC ACID; POTASSIUM SORBATE

Indecision™

Drug Facts

____________________________________________________________________________________________________________

HPUS active ingredients: Chamomilla, Clematis vitalba, flos, Croton tiglium, Curare, Dulcamara, Graphites, Ignatia amara, Iodium, Lathyrus sativus, Lonicera caprifolium, flos, Millefolium, Muriaticum acidum, Rosa damascena, Saccharum officinale, Silicea, Stigmata maidis. Equal volumes of each ingredient in 10X, 30X, 100X, 1LM, 2LM, 3LM, 5LM potencies.

INDICATIONS AND USAGE

Uses a natural aid for:

- indecisiveness
- irresolution
- dissatisfaction
- aversion to responsibility
- avoidance of high pressure situations
- fickleness

INACTIVE INGREDIENT

Inactive ingredients: Bio-Energetically Enhanced pure water base, citric acid, potassium sorbate.

Warnings

- Stop use and ask your doctor if symptoms persist or worsen.
- If pregnant or breast-feeding, take only on advice of a healthcare professional.

- Keep out of reach of children.

Directions:

- Initially, depress pump until primed.
- Spray one dose directly into mouth.
- Adults: 3 sprays 3 times per day.
- Children 2-12 years: 2 sprays 3 times per day.
- Use additionally as needed, up to 6 times per day.

OTHER SAFETY INFORMATION

Tamper resistant for your protection. Use only if safety seal is intact. This product has not been clinically tested.

PURPOSE

Uses a natural aid for: indecisiveness, irresolution, dissatisfaction, aversion to responsibility, avoidance of high pressure situations, fickleness.